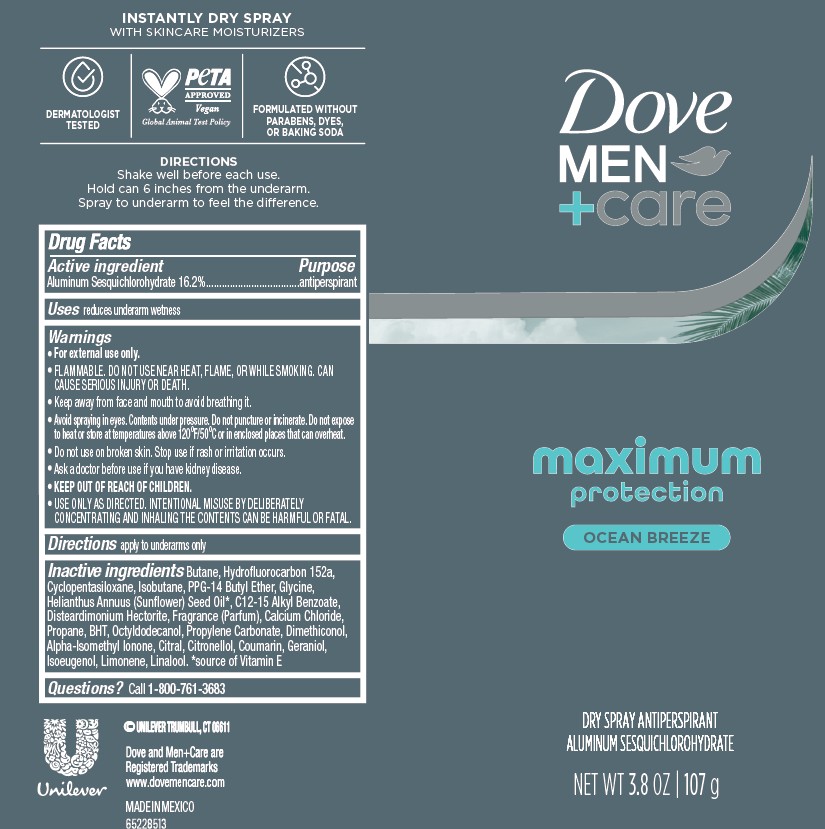 DRUG LABEL: Dove Men Care
NDC: 64942-2402 | Form: AEROSOL, SPRAY
Manufacturer: Conopco d/b/a Unilever
Category: otc | Type: HUMAN OTC DRUG LABEL
Date: 20251110

ACTIVE INGREDIENTS: ALUMINUM SESQUICHLOROHYDRATE 16.2 g/100 g
INACTIVE INGREDIENTS: COUMARIN; BHT; BUTANE; C12-15 ALKYL BENZOATE; GLYCINE; OCTYLDODECANOL; ISOEUGENOL; PROPANE; LINALOOL; PROPYLENE CARBONATE; CYCLOPENTASILOXANE; ISOBUTANE; PPG-14 BUTYL ETHER; HELIANTHUS ANNUUS (SUNFLOWER) SEED OIL; DISTEARDIMONIUM HECTORITE; CALCIUM CHLORIDE; ALPHA-ISOMETHYL IONONE; GERANIOL; CITRONELLOL; HYDROFLUOROCARBON 152A; DIMETHICONOL (40 CST); LIMONENE, (+/-)-; CITRAL

Dove Men Care Maximum Protection Ocean Breeze Dry Spray Deodorant

DESCRIPTION

Dove Men Care Maximum Protection Ocean Breeze Dry Spray Deodorant

ACTIVE INGREDIENT

Aluminum Sesquichlorohydrate 16.2%

PURPOSE

Antiperspirant

INDICATIONS AND USAGE

reduces underarm wetness

WARNINGS

• For external use only.
• FLAMMABLE. DO NOT USE NEAR HEAT, FLAME, OR WHILE SMOKING. CAN CAUSE SERIOUS INJURY OR DEATH.
• Keep away from face and mouth to avoid breathing it.
• Avoid spraying in eyes. Contents under pressure. Do not puncture or incinerate. Do not expose to heat or store at temperatures above 120°F/50°C or in enclosed places that can overheat.
• Do not use on broken skin. • Stop use if rash or irritation occurs.• Ask a doctor before use if you have kidney disease. • USE ONLY AS DIRECTED. INTENTIONAL MISUSE BY DELIBERATELY CONCENTRATING AND INHALING THE CONTENTS CAN BE HARMFUL OR FATAL.
Help stop inhalation abuse. For information visit www.inhalant.org

• KEEP OUT OF REACH OF CHILDREN.

DOSAGE AND ADMINISTRATION

apply to underarms only

INACTIVE INGREDIENT

Butane, Hydrofluorocarbon 152a, Cyclopentasiloxane, Isobutane, PPG-14 Butyl Ether, Glycine, Helianthus Annuus (Sunflower) Seed Oil, C12-15 Alkyl Benzoate, Disteardimonium Hectorite, Fragrance (Parfum), Calcium Chloride, Propane, BHT, Octyldodecanol, Propylene Carbonate, Dimethiconol, Alpha-Isomethyl Ionone, Citral, Citronellol, Coumarin, Geraniol, Isoeugenol, Limonene, Linalool.

QUESTIONS

Call 1-800-761-3683